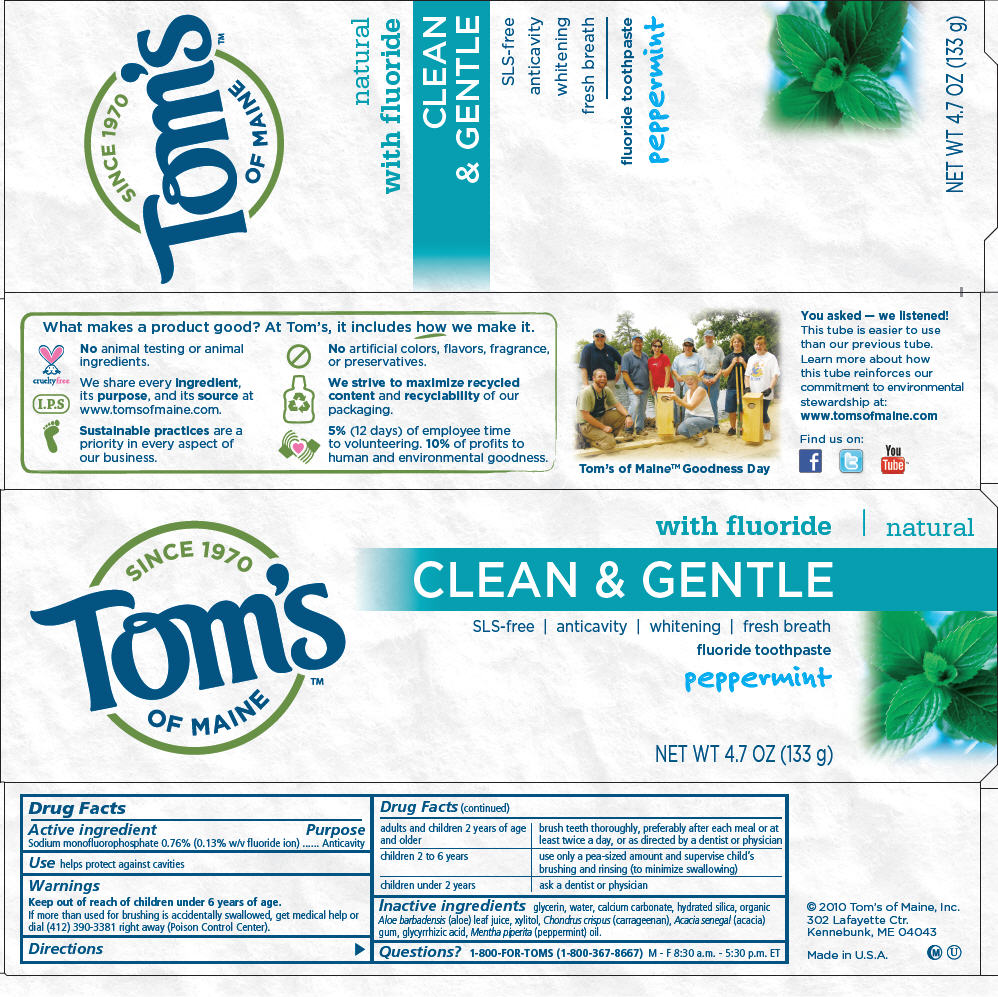 DRUG LABEL: Clean and Gentle 
NDC: 51009-107 | Form: PASTE, DENTIFRICE
Manufacturer: Tom's of Maine, Inc.
Category: otc | Type: HUMAN OTC DRUG LABEL
Date: 20110214

ACTIVE INGREDIENTS: Sodium Monofluorophosphate 0.0076 g/1 g
INACTIVE INGREDIENTS: Glycerin; Water; Calcium carbonate; Hydrated silica; Xylitol; Carrageenan; Peppermint Oil; Glycyrrhizin; Aloe Vera Leaf

Tom's
OF MAINE
CLEAN & GENTLE
fluoride toothpaste

Drug Facts

Active ingredient

Sodium monofluorophosphate 0.76% (0.13% w/v fluoride ion)

Purpose

Anticavity

Use

helps protect against cavities

Warnings

Keep out of reach of children under 6 years of age.

If more than used for brushing is accidentally swallowed, get medical help or dial (412) 390-3381 right away (Poison Control Center).

Directions

adults and children 2 years of age and older | brush teeth thoroughly, preferably after each meal or at least twice a day, or as directed by a dentist or physician
children 2 to 6 years | use only a pea-sized amount and supervise child's brushing and rinsing (to minimize swallowing)
children under 2 years | ask a dentist or physician

Inactive ingredients

glycerin, water, calcium carbonate, hydrated silica, organic Aloe barbadensis (aloe) leaf juice, xylitol, Chondrus crispus (carrageenan), Acacia senegal (acacia) gum, glycyrrhizic acid, Mentha piperita (peppermint) oil.

Questions?

1-800-FOR-TOMS (1-800-367-8667) M - F 8:30 a.m. - 5:30 p.m. ET

PRINCIPAL DISPLAY PANEL - 133 g Carton

SINCE 1970
Tom's
OF MAINE™

with fluoride | natural

CLEAN & GENTLE

SLS-free | anticavity | whitening | fresh breath
fluoride toothpaste

peppermint

NET WT 4.7 OZ (133 g)